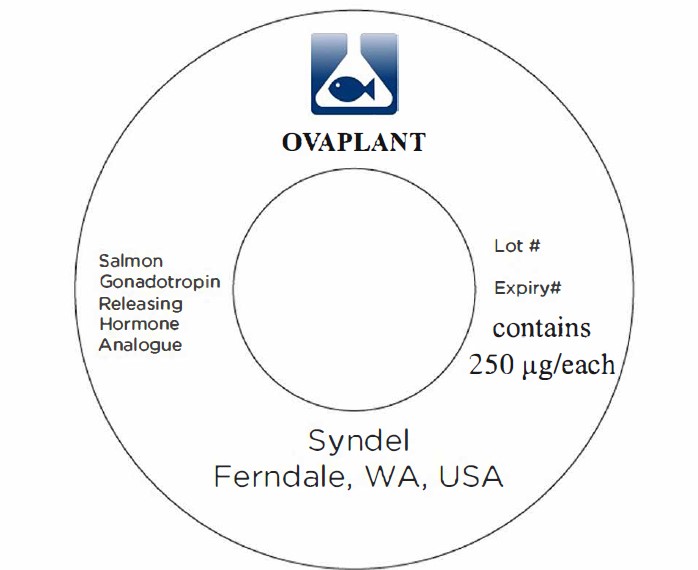 DRUG LABEL: Ovaplant
NDC: 50378-026 | Form: PELLET, IMPLANTABLE
Manufacturer: Western Chemical Inc.
Category: animal | Type: OTC ANIMAL DRUG LABEL
Date: 20241115

ACTIVE INGREDIENTS: SALMON GONADOTROPIN RELEASING HORMONE D-ARG6 ANALOG ETHYL AMIDE ACETATE 0.250 g/1 1
INACTIVE INGREDIENTS: WATER 9 L/1 1; CHOLESTEROL 42.375 g/1 1; CELLULOSE, MICROCRYSTALLINE 1.425 g/1 1; METHYLCELLULOSE (100 CPS) 1000 g/1 1; SILICON DIOXIDE 0.2500 g/1 1; MAGNESIUM STEARATE 0.2500 g/1 1

Ovaplant

Safety Precautions

Ovaplant™ contains a physiological agent used to stimulate ovulation or spermiation. Workers should avoid direct contact. Keep out of reach of children

Stability and Storage

Stored at refrigerated temperature (4°C) and out of direct sunlight, the shelf life of Ovaplant™ exceeds 18 months.

Reccomend Dose and Administration Method

- Injected as a single implant dose
- Can be injected immediately prior to the normal spawning season
- Spawning of groups can be advanced and synchronized
- Repeat injections can be given to fish treated long before normal spawning

Injecting Ovaplant™:

- Cleanliness - Ensure that all equipment is clean and, if possible, sterilized. Wear gloves.
- Injection - Inject using the Ralgun implanter into the dorsal sinus. Ensure that both males and females are injected at the same time. Inject Ovaplant™ carefully, and quickly remove the Ralgun needle. Gently place the fish into a container of fresh, aerated water.
- Recovery - After the fish has recovered from sedation (5 to 10 minutes), return it to the breeding tank. More than one fish may be induced at the same time.

Sedation for Handling: If sedation is required, use a plastic or glass tank of sufficient size to hold the fish. Anesthetize with TMS (MS222, Tricaine methanesulfonate) or Aquacalm at the recommended level, make sure to mix thoroughly BEFORE adding the fish. Always handle fish gently. Avoid contact between the anesthetic solution and eggs or milt.